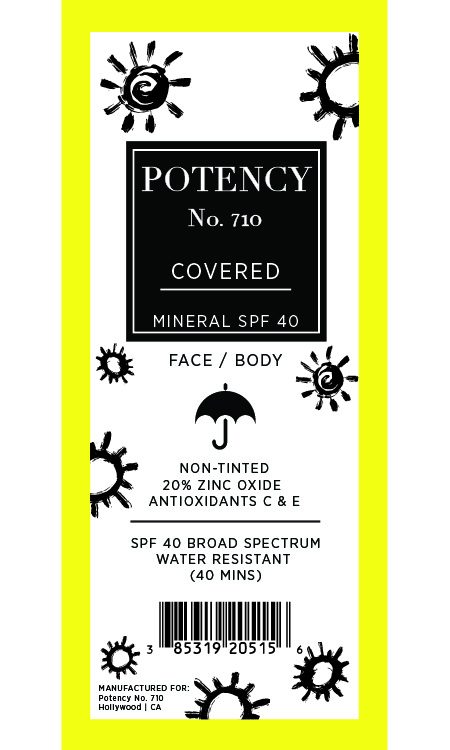 DRUG LABEL: COVERED
NDC: 85319-205 | Form: CREAM
Manufacturer: Potency No. 710 LLC
Category: otc | Type: HUMAN OTC DRUG LABEL
Date: 20251210

ACTIVE INGREDIENTS: ZINC OXIDE 200 mg/1 g
INACTIVE INGREDIENTS: GLYCERIN; HYDROGEN DIMETHICONE (20 CST); TRIETHANOLAMINE; DIMETHICONE; EDETATE DISODIUM ANHYDROUS; PEG-30 DIPOLYHYDROXYSTEARATE; POLYSORBATE 20; ALPHA-TOCOPHEROL ACETATE; C12-15 ALKYL BENZOATE; CETYL PEG/PPG-10/1 DIMETHICONE (HLB 4); STEARYL DIMETHICONE (400 MPA.S AT 50C); POLYHYDROXYSTEARIC ACID (2300 MW); TETRAHEXYLDECYL ASCORBATE; CAPRYLHYDROXAMIC ACID; CYCLOHEXASILOXANE; DIMETHICONE CROSSPOLYMER; DIMETHICONE/VINYL DIMETHICONE CROSSPOLYMER (SOFT PARTICLE); TRIETHOXYCAPRYLYLSILANE; CAPRYLYL GLYCOL; SODIUM CHLORIDE; WATER; CYCLOPENTASILOXANE; DIMETHICONOL (2000 CST); PEG-10 DIMETHICONE (600 CST); MICROCRYSTALLINE WAX; POLYGLYCERYL-4 ISOSTEARATE

Active Ingredients:

Zinc Oxide 20%

Purpose:

Sunscreen

Warning:

For external use only

Warning:

For external use only

Keep out of reach of children

Warning:

Keep out of reach of children

Directions:

Apply liberally 15 minutes before sun exposure

INACTIVE INGREDIENT

C12-15 Alkyl Benzoate, Caprylhydroxamic Acid, Caprylyl Glycol, Cetyl PEG/PPG-10/1 Dimethicone, Cyclohexasiloxane, Cyclopentasiloxane, Dimethicone, Dimethicone Crosspolymer, Dimethicone/Vinyl Dimethicone Crosspolymer, Dimethiconol, Disodium EDTA, Glycerin, Hydrogen Dimethicone, Microcrystalline Wax, PEG-10 Dimethicone, PEG-30 Dipolyhydroxystearate, Polyglyceryl-4 Isostearate, Polyhydroxystearic Acid, Polysorbate 20, Sodium Chloride, Stearyl Dimethicone, Tetrahexyldecyl Ascorbate, Tocopheryl Acetate, Triethanolamine, Triethoxycaprylylsilane, Water

OTHER SAFETY INFORMATION

SAMPLE NOT FOR RESALE